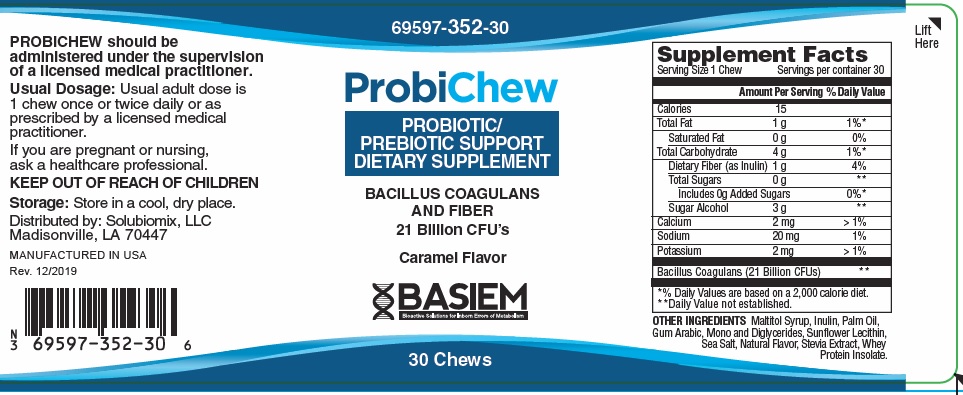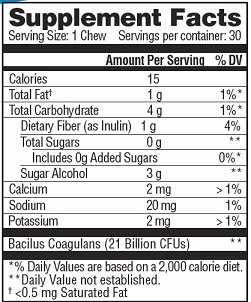 DRUG LABEL: Probichew
NDC: 69597-352 | Form: BAR, CHEWABLE
Manufacturer: Basiem, LLC
Category: other | Type: DIETARY SUPPLEMENT
Date: 20251006

ACTIVE INGREDIENTS: BACILLUS COAGULANS 21000000000 [CFU]/1 1; INULIN 1000 mg/1 1
INACTIVE INGREDIENTS: MALTITOL; PALM OIL; ACACIA; LECITHIN, SUNFLOWER; SEA SALT; STEVIA REBAUDIUNA LEAF; WHEY PROTEIN HYDROLYSATE; SODIUM; POTASSIUM; CALCIUM; MANNITOL

Probichew

STATEMENT OF IDENTITY

PROBICHEW Dietary Supplemement

Dispensed by Prescription

Amount Per Serving: |  | %DV
Bacillus Coagulans | 21 Billion | *
Dietary Fiber (as Inulin) | 1 gram | 4%
*Daily Values (DV) not established

OTHER INGREDIENTS: Sodium, Potassium, Calcium, Sugar Alcohol, Maltitol Syrup, Inulin, Palm Oil, Gum Arabic, Mono and Diglycerides, Sunflower Lecithin, Sea Salt, Natural Flavor, Stevia Extract, Whey Protein Isolate

PROBICHEW is an orally administered prescription probiotic/prebiotic formulation for the clinical dietary management of suboptimal nutritional status in patients where advanced supplementation is required and nutritional supplementation in physiologically stressful conditions for maintenance of good health is needed.

PROBICHEW should be administered under the supervision of a licensed medical practitioner.

PROBICHEW is manufactured in accordance with Current Good Manufacturing Practice for foods, using ingredients that have been approved by the U.S. Food and Drug Administration (FDA) as food additives or are Generally Recognized as Safe (GRAS) for their intended use

DOSAGE

Usual adult dose is 1 chew once or twice daily, or as prescribed by a licensed medical practitioner.

If you are pregnant or nursing, ask a healthcare professional.

PROBICHEW should be administered under the supervision of a licensed medical practitioner.

DIRECTIONS FOR USE: REMOVE FOIL BEFORE CONSUMING CHEW. Consume entire chew or as directed by a healthcare professional.

SAFE HANDLING

This product is contraindicated in patients with a known hypersensitivity to any of the ingredients.

PROBICHEW chews should only be used under the direction and supervision of a licensed medical practitioner. Use with caution in patients that may have a medical condition, are pregnant, lactating, trying to conceive, under the age of 18, or taking medications.

KEEP OUT OF REACH OF CHILDREN

STORAGE

Store at 20°-25°C (68°-77°F), excursions permitted to 15°-30°C (59°-86°F) [See USP Controlled Room Temperature.]

HOW SUPPLIED HEALTH CLAIM

PROBICHEW, Probiotic/Prebiotic Support

Dietary Supplement

Chews are beige in color and individually wrapped in a bronze and silver foil.

Bottles contain 30 Chews 69597-350-30*

Manufactured in USA for:
Basiem, LLC

Madisonville, LA 70447

Rev. 12/2019

*Basiem does not represent these product codes to be National Drug Codes (NDC). Product codes are formatted according to standard industry practice, to meet the formatting requirement by pedigree reporting and supply-chain control including pharmacies.

† The most appropriate way to ensure pedigree reporting consistent with these regulatory guidelines and safety monitoring is to dispense this product by prescription. This is not an Orange Book product. This product may be administered only under a physician’s supervision and all prescriptions using this product shall be pursuant to state statutes as applicable. The ingredients, indication or claims of this product are not to be construed to be drug claims.